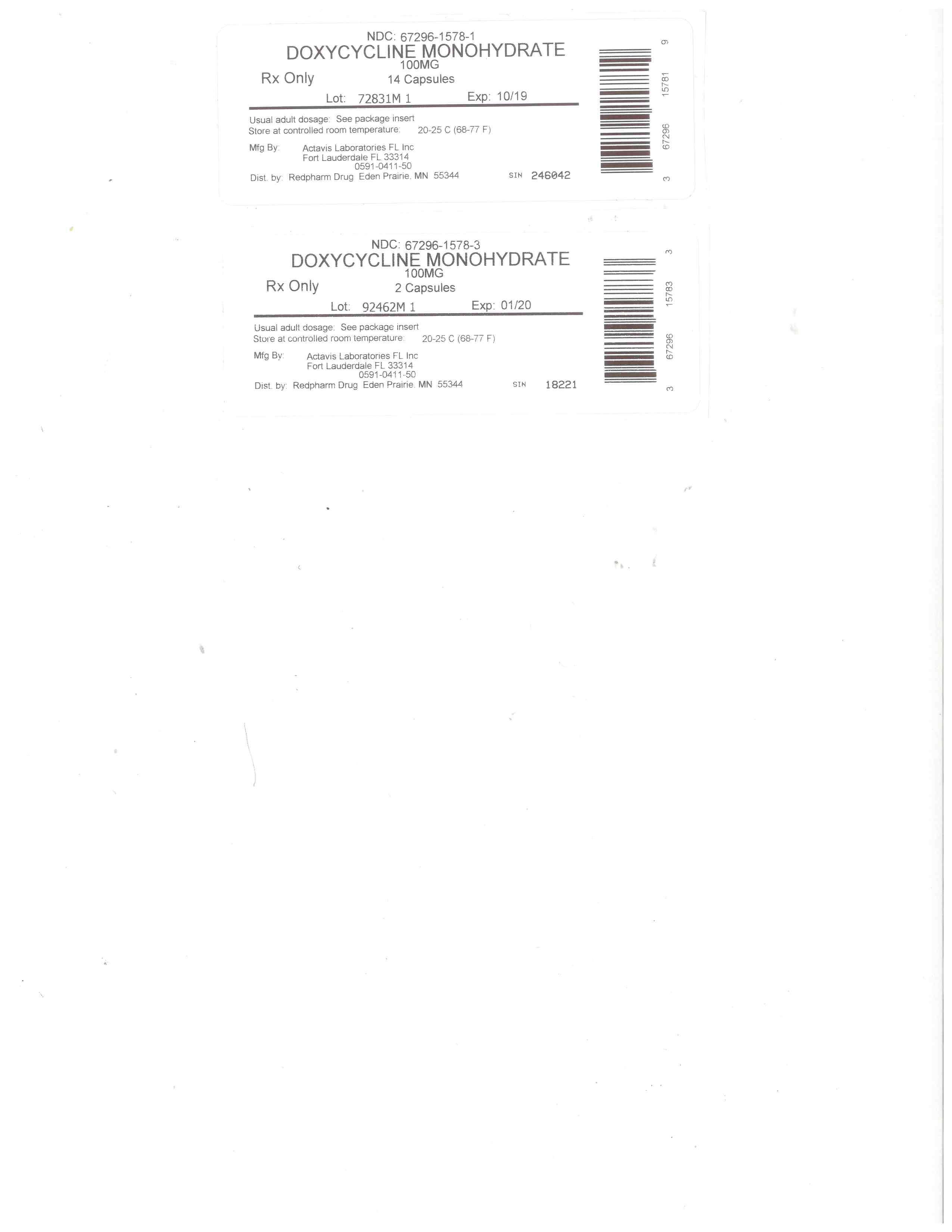 DRUG LABEL: Doxycycline Monohydrate
NDC: 67296-1578 | Form: CAPSULE
Manufacturer: RedPharm Drug, Inc.
Category: prescription | Type: HUMAN PRESCRIPTION DRUG LABEL
Date: 20200120

ACTIVE INGREDIENTS: DOXYCYCLINE 100 mg/1 1
INACTIVE INGREDIENTS: CELLULOSE, MICROCRYSTALLINE; MAGNESIUM STEARATE; FERRIC OXIDE YELLOW; SILICON DIOXIDE; TITANIUM DIOXIDE; FERRIC OXIDE RED; FERROSOFERRIC OXIDE; SODIUM STARCH GLYCOLATE TYPE A POTATO

doxy mono 100mg

SPL UNCLASSIFIED SECTION

To reduce the development of drug-resistant bacteria and maintain the effectiveness of doxycycline monohydrate capsules and other antibacterial drugs, doxycycline monohydrate capsules should be used only to treat or prevent infections that are proven or strongly suspected to be caused by bacteria.

DESCRIPTION

Doxycycline is a broad-spectrum antibacterial synthetically derived from oxytetracycline. Doxycycline monohydrate capsules 100 mg, 75 mg, and 50 mg capsules contain doxycycline monohydrate equivalent to 100 mg, 75 mg, or 50 mg of doxycycline for oral administration. The chemical designation of the light-yellow crystalline powder is alpha-6-deoxy-5-oxytetracycline.

Structural formula:

[Doxycycline structural formula.]

C22H24N2O8 • H2O M.W. = 462.45

Doxycycline has a high degree of lipid solubility and a low affinity for calcium binding. It is highly stable in normal human serum. Doxycycline will not degrade into an epianhydro form.

Inert ingredients: colloidal silicon dioxide; magnesium stearate; microcrystalline cellulose; sodium starch glycolate; and a hard gelatin capsule which contains black iron oxide, red iron oxide, titanium dioxide, and yellow iron oxide for the 100 mg and 75 mg strengths, titanium dioxide and yellow iron oxide for the 50 mg strength. The capsules are printed with edible ink containing black iron oxide, red iron oxide, and yellow iron oxide for the 50 mg and 100 mg strengths and black iron oxide, FD&C Blue No. 2, FD&C Red No. 40, FD&C Blue No. 1, and D&C Yellow No. 10 for the 75 mg strength.

CLOSE

CLINICAL PHARMACOLOGY

Tetracyclines are readily absorbed and are bound to plasma proteins in varying degrees. They are concentrated by the liver in the bile and excreted in the urine and feces at high concentrations in a biologically active form. Doxycycline is virtually completely absorbed after oral administration.

Following a 200 mg dose of doxycycline monohydrate, 24 normal adult volunteers averaged the following serum concentration values:

Time (hr): 0.5 1.0 1.5 2.0 3.0 4.0 8.0 12.0 24.0 48.0 72.0
Conc. 1.02 2.26 2.67 3.01 3.16 3.03 2.03 1.62 0.95 0.37 0.15 (μg/mL)

Average Observed Values
Maximum Concentration 3.61 μg/mL (± 0.9 sd)
Time of Maximum Concentration 2.60 hr (± 1.10 sd)
Elimination Rate Constant 0.049 per hr (± 0.030 sd)
Half-Life 16.33 hr (± 4.53 sd)

Excretion of doxycycline by the kidney is about 40%/72 hours in individuals with normal function (creatinine clearance about 75 mL/min). This percentage excretion may fall as low as 1-5%/72 hours in individuals with severe renal insufficiency (creatinine clearance below 10 mL/min). Studies have shown no significant difference in serum half-life of doxycycline (range 18-22 hours) in individuals with normal and severely impaired renal function.

Hemodialysis does not alter serum half-life.

Microbiology:

Mechanism of Action

Doxycycline inhibits bacterial protein synthesis by binding to the 30S ribosomal subunit. Doxycycline has bacteriostatic activity against a broad range of Gram-positive and Gram-negative bacteria. Cross resistance with other tetracyclines is common. Doxycycline has been shown to be active against most isolates of the following microorganisms, both in vitro and in clinical infections as described in the INDICATIONS AND USAGE section of the package insert for doxycycline monohydrate capsules.

Gram-Negative Bacteria
Acinetobacter species
Bartonella bacilliformis
Brucella species
Calymmatobacterium granulomatis
Campylobacter fetus
Enterobacter aerogenes
Escherichia coli
Francisella tularensis
Haemophilus ducreyi
Haemophilus influenzae
Klebsiella species
Neisseria gonorrhoeae
Shigella species
Vibrio cholerae
Yersinia pestis

Gram-Positive Bacteria
Bacillus anthracis
Streptococcus pneumoniae

Anaerobic Bacteria
Clostridium species
Fusobacterium fusiforme
Propionibacterium acnes

Other Bacteria
Nocardiae and other Actinomyces species
Borrelia recurrentis
Chlamydophila psittaci
Chlamydia trachomatis
Mycoplasma pneumoniae
Rickettsiae
Treponema pallidum
Treponema pertenue
Ureaplasma urealyticum

Parasites
Balantidium coli
Entamoeba species

Susceptibility Testing Methods
When available, the clinical microbiology laboratory should provide the results of in vitro susceptibility test results for antimicrobial drugs used in resident hospitals to the physician as periodic reports that describe the susceptibility profile of nosocomial and community-acquired pathogens. These reports should aid the physician in selecting the most effective antimicrobial.

Dilution techniques
Quantitative methods are used to determine antimicrobial minimum inhibitory concentrations (MICs). These MICs provide estimates of the susceptibility of bacteria to antimicrobial compounds. The MICs should be determined using a standardized test method (broth and/or agar).1,2,4 The MIC values should be interpreted according to criteria provided in Table 1.

Diffusion techniques
Quantitative methods that require measurement of zone diameters can also provide reproducible estimates of the susceptibility of bacteria to antimicrobial compounds. The zone size provides an estimate of the susceptibility of bacteria to antimicrobial compounds.

The zone size should be determined using a standardized test method.1,3,4 This procedure uses paper disks impregnated with 30 mcg doxycycline to test the susceptibility of microorganisms to doxycycline. The disk diffusion interpretive criteria are provided in Table 1.

Anaerobic Techniques
For anaerobic bacteria, the susceptibility to doxycycline can be determined by a standardized test method.5 The MIC values obtained should be interpreted according to the criteria provided in Table 1.

Table 1: Susceptibility Test Interpretive Criteria for Doxycycline and Tetracycline

*
Organisms susceptible to tetracycline are also considered susceptible to doxycycline. However, some organisms that are intermediate or resistant to tetracycline may be susceptible to doxycycline.
†

The current absence of resistance isolates precludes defining any results other than "Susceptible". If isolates yielding MIC results other than susceptible, they should be submitted to a reference laboratory for further testing.

‡
Gonococci with 30 mcg tetracycline disk zone diameters of less than 19 mm usually indicate a plasmid-mediated tetracycline resistant Neisseria gonorrhoeae isolate. Resistance in these strains should be confirmed by a dilution test (MIC ≥ 16 mcg per mL).

Bacteria* Minimal Inhibitory Concentration
(mcg per mL) Zone Diameter (mm) Agar Dilution (mcg per mL)
S I R S I R S I R
Acinetobacter spp.
Doxycycline ≤ 4 8 ≥ 16 ≥ 13 10 -12 ≤ 9 - - -
Tetracycline ≤ 4 8 ≥ 16 ≥ 15 12 - 14 ≤ 11 - - -
Anaerobes
Tetracycline - - - - - - ≤ 4 8 ≥ 16
Bacillus anthracis†
Doxycycline ≤ 1 - - - - - - - -
Tetracycline ≤ 1 - - - - - - - -
Brucellaspecies†
Doxycycline ≤ 1 - - - - - - - -
Tetracycline ≤ 1 - - - - - - - -
Enterobacteriaceae
Doxycycline ≤ 4 8 ≥ 16 ≥ 14 11 -13 ≤ 10 - - -
Tetracycline ≤ 4 8 ≥ 16 ≥ 15 12 -14 ≤11 - - -
Franciscella tularensis†
Doxycycline ≤ 4 - - - - - - - -
Tetracycline ≤ 4 - - - - - - - -
Haemophilus influenzae
Tetracycline ≤ 2 4 ≥ 8 ≥ 29 26 - 28 ≤ 25 - - -
Mycoplasma pneumoniae†
Tetracycline - - - - - - ≤ 2 - -
Neisseria gonorrhoeae‡
Tetracycline - - - ≥ 38 31 - 37 ≤ 30 ≤ 0.25 0.5 - 1 ≥ 2
Norcardiae and other aerobic Actinomycesspecies†
Doxycycline ≤ 1 2-4 ≥ 8 - - - - - -
Streptococcus pneumoniae
Tetracycline ≤ 2 4 ≥ 8 ≥ 23 19 - 22 ≤ 18 - - -
Vibrio cholerae
Doxycycline ≤ 4 8 ≥ 16 - - - - - -
Tetracycline ≤ 4 8 ≥ 16 - - - - - -
Yersinia pestis
Doxycycline ≤ 4 8 ≥ 16 - - - - - -
Tetracycline ≤ 4 8 ≥ 16 - - - - - -
Ureaplasma urealyticum
Tetracycline - - - - - - ≤ 1 - ≥ 2

A report of Susceptible (S) indicates that the antimicrobial is likely to inhibit growth of the pathogen if the antimicrobial compound reaches the concentrations at the infection site necessary to inhibit growth of the pathogen. A report of Intermediate (I) indicates that the result should be considered equivocal, and, if the bacteria is not fully susceptible to alternative, clinically feasible drugs, the test should be repeated. This category implies possible clinical applicability in body sites where the drug product is physiologically concentrated or in situations where high dosage of drug can be used. This category also provides a buffer zone that prevents small uncontrolled technical factors from causing major discrepancies in interpretation. A report of Resistant (R) indicates that the antimicrobial is not likely to inhibit growth of the pathogen if the antimicrobial compound reaches the concentrations usually achievable at the infection site; other therapy should be selected.

Quality Control

Standardized susceptibility test procedures require the use of laboratory controls to monitor and ensure the accuracy and precision of the supplies and reagents used in the assay, and the techniques of the individuals performing the test.1,2,3,4,5,6,7 Standard doxycycline and tetracycline powders should provide the following range of MIC values noted in Table 2. For the diffusion technique using the 30 mcg doxycycline disk the criteria noted in Table 2 should be achieved.

Table 2: Acceptable Quality Control Ranges for Susceptibility Testing for Doxycycline and Tetracycline
QC Strain Minimal Inhibitory Concentration (mcg per mL) Zone Diameter (mm) Agar Dilution
(mcg per mL)
Enterococcus faecalisATCC 29212
Doxycycline 2 - 8 - -
Tetracycline 8 - 32 - -
Escherichia coli ATCC 25922
Doxycycline 0.5 - 2 18 - 24 -
Tetracycline 0.5 - 2 18 - 25 -
Haemophilus influenzae ATCC 49247
Tetracycline 4 - 32 14 - 22 -
Neisseria gonorrhoeae ATCC 49226
Tetracycline - 30 - 42 0.25 - 1
Staphylococcus aureus ATCC 25923
Doxycycline - 23 - 29 -
Tetracycline - 24 - 30 -
Staphylococcus aureus ATCC 29213
Doxycycline 0.12 - 0.5 - -
Tetracycline 0.12 - 1 - -
Streptococcus pneumoniae ATCC 49619
Doxycycline 0.015 - 0.12 25 - 34 -
Tetracycline 0.06 - 0.5 27 - 31 -
Bacteroides fragilis ATCC 25285
Tetracycline - - 0.125 - 0.5
Bacteroides thetaiotaomicron ATCC 29741
Tetracycline - - 8 - 32
Mycoplasma pneumoniae ATCC 29342
Tetracycline 0.06 - 0.5 - 0.06 - 0.5
Ureaplasma urealyticum ATCC 33175
Tetracycline - - ≥ 8

INDICATIONS AND USAGE

To reduce the development of drug-resistant bacteria and maintain effectiveness of doxycycline monohydrate capsules and other antibacterial drugs, doxycycline monohydrate capsules should be used only to treat or prevent infections that are proven or strongly suspected to be caused by susceptible bacteria. When culture and susceptibility information are available, they should be considered in selecting or modifying antibacterial therapy. In the absence of such data, local epidemiology and susceptibility patterns may contribute to the empiric selection of therapy.

Doxycycline is indicated for the treatment of the following infections:
Rocky mountain spotted fever, typhus fever and the typhus group, Q fever, rickettsialpox, and tick fevers caused by Rickettsiae.
Respiratory tract infections caused by Mycoplasma pneumoniae.
Lymphogranuloma venereum caused by Chlamydia trachomatis.
Psittacosis (ornithosis) caused by Chlamydophila psittaci.
Trachoma caused by Chlamydia trachomatis, although the infectious agent is not always eliminated as judged by immunofluorescence.
Inclusion conjunctivitis caused by Chlamydia trachomatis.
Uncomplicated urethral, endocervical or rectal infections in adults caused by Chlamydia trachomatis.
Nongonococcal urethritis caused by Ureaplasma urealyticum.
Relapsing fever due to Borrelia recurrentis.

Doxycycline is also indicated for the treatment of infections caused by the following gram-negative microorganisms:
Chancroid caused by Haemophilus ducreyi.
Plague due to Yersinia pestis.
Tularemia due to Francisella tularensis.
Cholera caused by Vibrio cholerae.
Campylobacter fetus infections caused by Campylobacter fetus.
Brucellosis due to Brucella species (in conjunction with streptomycin).
Bartonellosis due to Bartonella bacilliformis.
Granuloma inguinale caused by Calymmatobacterium granulomatis.

Because many strains of the following groups of microorganisms have been shown to be resistant to doxycycline, culture and susceptibility testing are recommended.

Doxycycline is indicated for treatment of infections caused by the following gram-negative microorganisms, when bacteriologic testing indicates appropriate susceptibility to the drug:
Escherichia coli
Enterobacter aerogenes
Shigella species
Acinetobacter species
Respiratory tract infections caused by Haemophilus influenzae.
Respiratory tract and urinary tract infections caused by Klebsiella species.

Doxycycline is indicated for treatment of infections caused by the following gram-positive microorganisms when bacteriologic testing indicates appropriate susceptibility to the drug:
Upper respiratory infections caused by Streptococcus pneumoniae.
Anthrax due to Bacillus anthracis, including inhalational anthrax (post-exposure): to reduce the incidence or progression of disease following exposure to aerosolized Bacillus anthracis.

When penicillin is contraindicated, doxycycline is an alternative drug in the treatment of the following infections:
Uncomplicated gonorrhea caused by Neisseria gonorrhoeae.
Syphilis caused by Treponema pallidum.
Yaws caused by Treponema pertenue.
Listeriosis due to Listeria monocytogenes.
Vincent’s infection caused by Fusobacterium fusiforme.
Actinomycosis caused by Actinomyces israelii.
Infections caused by Clostridium species.

In acute intestinal amebiasis, doxycycline may be a useful adjunct to amebicides.

In severe acne, doxycycline may be useful adjunctive therapy.

CONTRAINDICATIONS

This drug is contraindicated in persons who have shown hypersensitivity to any of the tetracyclines.

WARNINGS

THE USE OF DRUGS OF THE TETRACYCLINE CLASS DURING TOOTH DEVELOPMENT (LAST HALF OF PREGNANCY, INFANCY, AND CHILDHOOD TO THE AGE OF 8 YEARS) MAY CAUSE PERMANENT DISCOLORATION OF THE TEETH (YELLOW-GRAY-BROWN). This adverse reaction is more common during long-term use of the drugs but has been observed following repeated short-term courses. Enamel hypoplasia has also been reported. TETRACYCLINE DRUGS, THEREFORE, SHOULD NOT BE USED IN THIS AGE GROUP, EXCEPT FOR ANTHRAX, INCLUDING INHALATIONAL ANTHRAX (POST-EXPOSURE), UNLESS OTHER DRUGS ARE NOT LIKELY TO BE EFFECTIVE OR ARE CONTRAINDICATED.

Clostridium difficile associated diarrhea (CDAD) has been reported with use of nearly all antibacterial agents, including doxycycline monohydrate capsules, and may range in severity from mild diarrhea to fatal colitis. Treatment with antibacterial agents alters the normal flora of the colon leading to overgrowth of C. difficile.

C. difficile produces toxins A and B which contribute to the development of CDAD. Hypertoxin producing strains of C. difficile cause increased morbidity and mortality, as these infections can be refractory to antimicrobial therapy and may require colectomy. CDAD must be considered in all patients who present with diarrhea following antibiotic use. Careful medical history is necessary since CDAD has been reported to occur over two months after the administration of antibacterial agents.

If CDAD is suspected or confirmed, ongoing antibiotic use not directed against C. difficile may need to be discontinued. Appropriate fluid and electrolyte management, protein supplementation, antibiotic treatment of C. difficile, and surgical evaluation should be instituted as clinically indicated.

All tetracyclines form a stable calcium complex in any bone-forming tissue. A decrease in the fibula growth rate has been observed in prematures given oral tetracycline in doses of 25 mg/kg every six hours. This reaction was shown to be reversible when the drug was discontinued.

Results of animal studies indicate that tetracyclines cross the placenta, are found in fetal tissues, and can have toxic effects on the developing fetus (often related to retardation of skeletal development). Evidence of embryo toxicity has been noted in animals treated early in pregnancy. If any tetracycline is used during pregnancy or if the patient becomes pregnant while taking these drugs, the patient should be apprised of the potential hazard to the fetus.

The antianabolic action of the tetracyclines may cause an increase in BUN. Studies to date indicate that this does not occur with the use of doxycycline in patients with impaired renal function.

Photosensitivity manifested by an exaggerated sunburn reaction has been observed in some individuals taking tetracyclines. Patients apt to be exposed to direct sunlight or ultraviolet light should be advised that this reaction can occur with tetracycline drugs, and treatment should be discontinued at the first evidence of skin erythema.

PRECAUTIONS

General:

As with other antibacterial preparations, use of this drug may result in overgrowth of non-susceptible organisms, including fungi. If superinfection occurs, doxycycline monohydrate capsules should be discontinued and appropriate therapy instituted.

Intracranial hypertension (IH, pseudotumor cerebri) has been associated with the use of tetracyclines including doxycycline monohydrate capsules. Clinical manifestations of IH include headache, blurred vision, diplopia, and vision loss; papilledema can be found on fundoscopy. Women of childbearing age who are overweight or have a history of IH are at greater risk for developing tetracycline associated IH. Concomitant use of isotretinoin and doxycycline monohydrate capsules should be avoided because isotretinoin is also known to cause pseudotumor cerebri.

Although IH typically resolves after discontinuation of treatment, the possibility for permanent visual loss exists. If visual disturbance occurs during treatment, prompt ophthalmologic evaluation is warranted. Since intracranial pressure can remain elevated for weeks after drug cessation patients should be monitored until they stabilize.

Incision and drainage or other surgical procedures should be performed in conjunction with antibacterial therapy when indicated.

Prescribing doxycycline monohydrate capsules in the absence of proven or strongly suspected bacterial infection or a prophylactic indication is unlikely to provide benefit to the patient and increases the risk of the development of drug-resistant bacteria.

Information for Patients:

All patients taking doxycycline should be advised:

–to avoid excessive sunlight or artificial ultraviolet light while receiving doxycycline and to discontinue therapy if phototoxicity (e.g., skin eruptions, etc.) occurs. Sunscreen or sunblock should be considered. (See WARNINGS.)

–to drink fluids liberally along with doxycycline to reduce the risk of esophageal irritation and ulceration. (See ADVERSE REACTIONS.)

–that the absorption of tetracyclines is reduced when taken with foods, especially those which contain calcium. However, the absorption of doxycycline is not markedly influenced by simultaneous ingestion of food or milk. (See DRUG INTERACTIONS.)

–that the absorption of tetracyclines is reduced when taking bismuth subsalicylate. (See DRUG INTERACTIONS.)

–not to use outdated or poorly stored doxycycline.

–that the use of doxycycline might increase the incidence of vaginal candidiasis.

Diarrhea is a common problem caused by antibiotics which usually ends when the antibiotic is discontinued. Sometimes after starting treatment with antibiotics, patients can develop watery and bloody stools (with or without stomach cramps and fever) even as late as two or more months after having taken the last dose of the antibiotic. If this occurs, patients should contact their physician as soon as possible.

Patients should be counseled that antibacterial drugs including doxycycline monohydrate capsules should only be used to treat bacterial infections. They do not treat viral infections (e.g., the common cold). When doxycycline monohydrate capsules are prescribed to treat a bacterial infection, patients should be told that although it is common to feel better early in the course of therapy, the medication should be taken exactly as directed. Skipping doses or not completing the full course of therapy may (1) decrease the effectiveness of the immediate treatment and (2) increase the likelihood that bacteria will develop resistance and will not be treatable by doxycycline monohydrate capsules or other antibacterial drugs in the future.

Laboratory Tests:

In venereal disease when coexistent syphilis is suspected, a dark-field examination should be done before treatment is started and the blood serology repeated monthly for at least four months.

In long-term therapy, periodic laboratory evaluations of organ systems, including hematopoietic, renal, and hepatic studies should be performed.

Drug Interactions:

Because tetracyclines have been shown to depress plasma prothrombin activity, patients who are on anticoagulant therapy may require downward adjustment of their anticoagulant dosage.

Since bacteriostatic drugs may interfere with the bactericidal action of penicillin, it is advisable to avoid giving tetracyclines in conjunction with penicillin.

Absorption of tetracyclines is impaired by antacids containing aluminum, calcium, or magnesium, and iron-containing preparations.

Barbiturates, carbamazepine, and phenytoin decrease the half-life of doxycycline.

The concurrent use of tetracycline and methoxyflurane has been reported to result in fatal renal toxicity.

Concurrent use of tetracycline may render oral contraceptives less effective.

Drug/Laboratory Test Interactions:

False elevations of urinary catecholamine levels may occur due to interference with the fluorescence test.

Carcinogenesis, Mutagenesis, Impairment of Fertility:

Long-term studies in animals to evaluate the carcinogenic potential of doxycycline have not been conducted. However, there has been evidence of oncogenic activity in rats in studies with related antibacterial, oxytetracycline (adrenal and pituitary tumors) and minocycline (thyroid tumors). Likewise, although mutagenicity studies of doxycycline have not been conducted, positive results in in vitromammalian cell assays have been reported for related antibacterial (tetracycline, oxytetracycline). Doxycycline administered orally at dosage levels as high as 250 mg/kg/day had no apparent effect on the fertility of female rats. Effect on male fertility has not been studied.

Pregnancy:

Teratogenic Effects.

Pregnancy Category D:

There are no adequate and well-controlled studies on the use of doxycycline in pregnant short-term, first trimester exposure. There are no human data available to assess the effects of long-term therapy of doxycycline in pregnant women such as that proposed for treatment of anthrax exposure. An expert review of published data on experiences with doxycycline use during pregnancy by TERIS - the Teratogen Information System - concluded that therapeutic doses during pregnancy are unlikely to pose a substantial teratogenic risk (the quantity and quality of data were assessed as limited to fair), but the data are insufficient to state that there is no risk.8
A case-control study (18,515 mothers of infants with congenital anomalies and 32,804 mothers of infants with no congenital anomalies) shows a weak but marginally statistically significant association with total malformations and use of doxycycline anytime during pregnancy. (Sixty-three [0.19%] of the controls and 56 [0.30%] of the cases were treated with doxycycline.) This association was not seen when the analysis was confined to maternal treatment during the period of organogenesis (i.e., in the second and third months of gestation) with the exception of a marginal relationship with neural tube defect based on only two exposed cases.9

A small prospective study of 81 pregnancies describes 43 pregnant women treated for 10 days with doxycycline during early first trimester. All mothers reported their exposed infants were normal at 1 year of age.10

Labor and Delivery:

The effect of tetracyclines on labor and delivery is unknown.

Nursing Mothers:

Tetracyclines are excreted in human milk, however, the extent of absorption of tetracyclines, including doxycycline, by the breastfed infant is not known. Short-term use by lactating women is not necessarily contraindicated; however, the effects of prolonged exposure to doxycycline in breast milk are unknown.11 Because of the potential for adverse reactions in nursing infants from doxycycline, a decision should be made whether to discontinue nursing or to discontinue the drug, taking into account the importance of the drug to the mother. (See WARNINGS.)

Pediatric Use:

See WARNINGS and DOSAGE AND ADMINISTRATION sections.

ADVERSE REACTIONS

Due to oral doxycycline’s virtually complete absorption, side effects to the lower bowel, particularly diarrhea, have been infrequent. The following adverse reactions have been observed in patients receiving tetracyclines.

Gastrointestinal: Anorexia, nausea, vomiting, diarrhea, glossitis, dysphagia, enterocolitis, and inflammatory lesions (with monilial overgrowth) in the anogenital region. Hepatotoxicity has been reported. These reactions have been caused by both the oral and parenteral administration of tetracyclines. Rare instances of esophagitis and esophageal ulcerations have been reported in patients receiving capsule and tablet forms of drugs in the tetracycline class. Most of these patients took medications immediately before going to bed. (See DOSAGE AND ADMINISTRATION.)

Skin: Maculopapular and erythematous rashes, Stevens-Johnson syndrome, toxic epidermal necrolysis, and erythema multiforme have been reported. Exfoliative dermatitis has been reported but is uncommon. Photosensitivity is discussed above. (See WARNINGS.)

Renal Toxicity: Rise in BUN has been reported and is apparently dose related. (See WARNINGS.)

Hypersensitivity Reactions: Urticaria, angioneurotic edema, anaphylaxis, anaphylactoid purpura, serum sickness, pericarditis, and exacerbation of systemic lupus erythematosus.

Blood: Hemolytic anemia, thrombocytopenia, neutropenia, and eosinophilia have been reported with tetracyclines.

Other: Intracranial hypertension (IH, pseudotumor cerebri) has been associated with the use of tetracyclines. (See PRECAUTIONS-GENERAL.)

When given over prolonged periods, tetracyclines have been reported to produce brown-black microscopic discoloration of the thyroid gland. No abnormalities of thyroid function are known to occur.

OVERDOSAGE

In case of overdosage, discontinue medication, treat symptomatically and institute supportive measures. Dialysis does not alter serum half-life, and it would not be of benefit in treating cases of overdosage.

DOSAGE AND ADMINISTRATION

THE USUAL DOSAGE AND FREQUENCY OF ADMINISTRATION OF DOXYCYCLINE DIFFERS FROM THAT OF THE OTHER TETRACYCLINES. EXCEEDING THE RECOMMENDED DOSAGE MAY RESULT IN AN INCREASED INCIDENCE OF SIDE EFFECTS.

Adults: The usual dose of oral doxycycline is 200 mg on the first day of treatment (administered 100 mg every 12 hours or 50 mg every 6 hours) followed by a maintenance dose of 100 mg/day. The maintenance dose may be administered as a single dose or as 50 mg every 12 hours. In the management of more severe infections (particularly chronic infections of the urinary tract), 100 mg every 12 hours is recommended.

For pediatric patients above eight years of age: The recommended dosage schedule for pediatric patients weighing 100 pounds or less is 2 mg/lb of body weight divided into two doses on the first day of treatment, followed by 1 mg/lb of body weight given as a single daily dose or divided into two doses, on subsequent days. For more severe infections up to 2 mg/lb of body weight may be used. For pediatric patients over 100 pounds the usual adult dose should be used.

Uncomplicated gonococcal infections in adults (except anorectal infections in men): 100 mg, by mouth, twice a day for 7 days. As an alternate single visit dose, administer 300 mg stat followed in one hour by a second 300 mg dose.

Acute epididymo-orchitis caused by N. gonorrhoeae: 100 mg, by mouth, twice a day for at least 10 days.

Primary and secondary syphilis: 300 mg a day in divided doses for at least 10 days.

Uncomplicated urethral, endocervical, or rectal infection in adults caused by Chlamydia trachomatis:100 mg, by mouth, twice a day for at least 7 days.

Nongonococcal urethritis caused by C. trachomatis and U. urealyticum: 100 mg, by mouth, twice a day for at least 7 days.

Acute epididymo-orchitis caused by C. trachomatis: 100 mg, by mouth, twice a day for at least 10 days.

Inhalational anthrax (post-exposure): ADULTS: 100 mg of doxycycline, by mouth, twice a day for 60 days. CHILDREN: weighing less than 100 pounds (45 kg); 1 mg/lb (2.2 mg/kg) of body weight, by mouth, twice a day for 60 days. Children weighing 100 pounds or more should receive the adult dose.

When used in streptococcal infections, therapy should be continued for 10 days.

Administration of adequate amounts of fluid along with capsule and tablet forms of drugs in the tetracycline class is recommended to wash down the drugs and reduce the risk of esophageal irritation and ulceration. (See ADVERSE REACTIONS.) If gastric irritation occurs, doxycycline may be given with food. Ingestion of a high fat meal has been shown to delay the time to peak plasma concentrations by an average of one hour and 20 minutes. However, in the same study, food enhanced the average peak concentration by 7.5% and the area under the curve by 5.7%.

HOW SUPPLIED

Doxycycline monohydrate capsules 50 mg have a white opaque body with an ivory opaque cap. The capsule bears the inscription WATSON 410 in brown and 50 mg in brown. Each capsule contains doxycycline monohydrate equivalent to 50 mg of doxycycline, supplied in bottles of 100.

Doxycycline monohydrate capsules 75 mg have a white opaque body with a brown opaque cap. The capsule bears the inscription MONODOX 75 in black and M 075 mg in black. Each capsule contains doxycycline monohydrate equivalent to 75 mg of doxycycline, supplied in bottles of 100.

Doxycycline Monohydrate Capsules 100 mg have an ivory opaque body with a brown opaque cap. The capsule bears the inscription WATSON 411 in white and 100 mg in brown. Each capsule contains doxycycline monohydrate equivalent to 100 mg of doxycycline, supplied in bottles of 50.

STORE AT 20° - 25°C (68° -77°F) WITH EXCURSIONS PERMITTED TO 15°C TO 30°C (59° TO 86°F). [SEE USP CONTROLLED ROOM TEMPERATURE.]
DISPENSE IN A TIGHT LIGHT-RESISTANT CONTAINER AS DEFINED IN THE USP/NF.

ANIMAL PHARMACOLOGY AND ANIMAL TOXICOLOGY

Hyperpigmentation of the thyroid has been produced by members of the tetracycline class in the following species: in rats by oxytetracycline, doxycycline, tetracycline PO4, and methacycline; in minipigs by doxycycline, minocycline, tetracycline PO4, and methacycline; in dogs by doxycycline and minocycline; in monkeys by minocycline.

Minocycline, tetracycline PO4, methacycline, doxycycline, tetracycline base, oxytetracycline HCl and tetracycline HCl were goitrogenic in rats fed a low iodine diet. This goitrogenic effect was accompanied by high radioactive iodine uptake. Administration of minocycline also produced a large goiter with high radioiodine uptake in rats fed a relatively high iodine diet.

Treatment of various animal species with this class of drugs has also resulted in the induction of thyroid hyperplasia in the following: in rats and dogs (minocycline), in chickens (chlortetracycline) and in rats and mice (oxytetracycline). Adrenal gland hyperplasia has been observed in goats and rats treated with oxytetracycline.

REFERENCES

1. Clinical and Laboratory Standards Institute (CLSI). Performance Standards for Antimicrobial Susceptibility Testing; Twenty-third Informational Supplement, CLSI document M100-S23,Clinical Laboratory Standards Institute, 950 West Valley Road, Suite 2500, Wayne Pennsylvania 19087, USA, 2013.

2. Clinical and Laboratory Standards Institute (CLSI). Methods for Dilution Antimicrobial Susceptibility Tests for Bacteria that Grow Aerobically; Approved Standard – Ninth Edition. CLSI document M07-A9, Clinical Laboratory Standards Institute, 950 West Valley Road, Suite 2500, Wayne Pennsylvania 19087, USA, 2012.

3. Clinical and Laboratory Standards Institute (CLSI). Performance Standards for Antimicrobial Disk Diffusion Susceptibility Tests; Approved Standard – Eleventh Edition. CLSI document M02-A11, Clinical Laboratory Standards Institute, 950 West Valley Road, Suite 2500, Wayne Pennsylvania 19087, USA, 2012.

4. Clinical and Laboratory Standards Institute (CLSI). Methods for Antimicrobial Dilution and Disk Susceptibility Testing of Infrequently Isolated or Fastidious Bacteria; Approved Guideline – Second Edition. CLSI document M45-A2, Clinical Laboratory Standards Institute, 950 West Valley Road, Suite 2500, Wayne Pennsylvania 19087, USA, 2010.

5. Clinical and Laboratory Standards Institute (CLSI). Methods for Antimicrobial Susceptibility Testing of Anaerobic Bacteria; Approved Standard – Eighth Edition. CLSI document M11-A8, Clinical Laboratory Standards Institute, 950 West Valley Road, Suite 2500, Wayne Pennsylvania 19087, USA, 2012.

6. Clinical and Laboratory Standards Institute (CLSI). Methods for Mycobacteria, Nocardiae, and Other Aerobic Actinomycetes; Approved Standard – Second Edition. CLSI document M24-A2, Clinical Laboratory Standards Institute, 950 West Valley Road, Suite 2500, Wayne Pennsylvania 19087, USA, 2011.

7. Clinical and Laboratory Standards Institute (CLSI). Methods for Antimicrobial Susceptibility Testing for Human Mycoplasmas; Approved Guideline. CLSI document M43-A, Clinical Laboratory Standards Institute, 950 West Valley Road, Suite 2500, Wayne Pennsylvania 19087, USA, 2011.

8. Friedman JM and Polifka JE. Teratogenic Effects of Drugs. A Resource for Clinicians (TERIS). Baltimore, MD: The Johns Hopkins University Press: 2000: 149-195.

9. Cziezel AE and Rockenbauer M. Teratogenic study of doxycycline. Obstet Gynecol 1997;89:524-528.

10. Horne HW Jr. and Kundsin RB. The role of mycoplasma among 81 consecutive pregnancies: a prospective study. Int J Fertil 1980; 25:315-317.

11. Hale T. Medications and Mothers Milk. 9th edition. Amarillo, TX: Pharmasoft Publishing 2000; 225-226.

Rx only

For all medical inquiries contact:
ACTAVIS
Medical Communications
Parsippany, NJ 07054
1-800-272-5525

Manufactured By:
Actavis Laboratories FL, Inc.
Fort Lauderdale, FL 33314 USA

Distributed By:
Actavis Pharma, Inc.
Parsippany, NJ 07054 USA

Content Updated: July 2014

191157-6